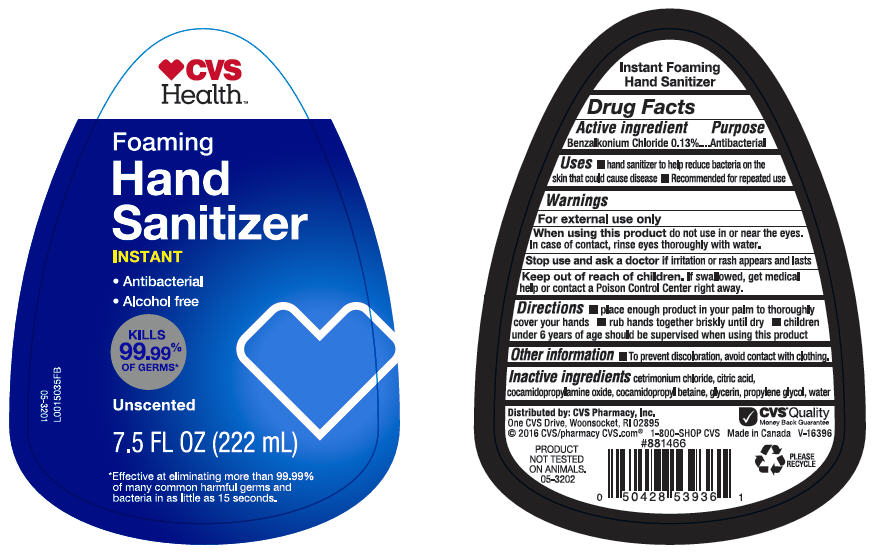 DRUG LABEL: CVS Foaming Hand Sanitizer 
NDC: 69842-584 | Form: LIQUID
Manufacturer: CVS Health
Category: otc | Type: HUMAN OTC DRUG LABEL
Date: 20220125

ACTIVE INGREDIENTS: Benzalkonium Chloride 1.3 mg/1 mL
INACTIVE INGREDIENTS: Cetrimonium Chloride; Citric Acid Monohydrate; Cocamidopropylamine Oxide; Cocamidopropyl Betaine; Glycerin; Propylene Glycol; Water

CVS Foaming Hand Sanitizer
Antibacterial

Active ingredients

Benzalkonium Chloride 0.13

Purpose

Antibacterial

Uses

♦ hand sanitizer to help reduce bacteria on the skin that could cause disease
♦ Recommended for repeated use

Warnings

For external use only

When using this product do not use in or near the eyes. In case of contact, rinse eyes thoroughly with water.

Stop use and ask a doctor if irritation or rash appears and lasts

Keep out of reach of children. If swallowed, get medical help or contact a Poison Control Center right away.

Directions

♦ place enough product in your palm to thoroughly cover your hands
♦ rub hands together briskly until dry
♦ children under 6 years of age should be supervised when using this product

Other information

♦ To prevent discoloration, avoid contact with clothing.

Inactive ingredients

Cetrimonium Chloride, Citric Acid, Cocamidopropylamine Oxide, Cocamidopropyl Betaine, Glycerin, Propylene Glycol, Water.

Distributed by: CVS Pharmacy, Inc.
One CVS Drive, Woonsocket, RI 02895

PRINCIPAL DISPLAY PANEL - 222 mL Bottle Label

♥CVS
Health™

Foaming
Hand
Sanitizer

INSTANT

- Antibacterial
- Alcohol free

KILLS
99.99%
OF GERMS*

Unscented

7.5 FL OZ (222 mL)

*Effective at eliminating more than 99.99%
or many common harmful germs and
bacteria in as little as 15 seconds.

05-3201
L0015035FB